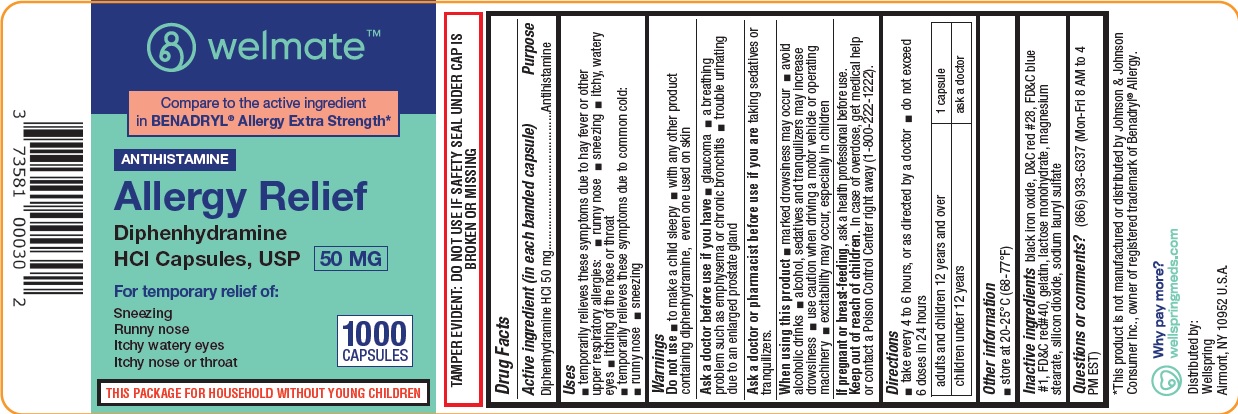 DRUG LABEL: Allergy Relief Diphenhydramine HCL 50 MG
NDC: 73581-020 | Form: CAPSULE
Manufacturer: YYBA Corporation
Category: otc | Type: HUMAN OTC DRUG LABEL
Date: 20260114

ACTIVE INGREDIENTS: DIPHENHYDRAMINE HYDROCHLORIDE 50 mg/1 1
INACTIVE INGREDIENTS: FERROSOFERRIC OXIDE; D&C RED NO. 28; FD&C BLUE NO. 1; FD&C RED NO. 40; GELATIN; LACTOSE MONOHYDRATE; MAGNESIUM STEARATE; SILICON DIOXIDE; SODIUM LAURYL SULFATE

Welmate Diphenhydramine 50 mg 73581-020

Active ingredient (in each banded capsule)

Diphenhydramine HCL 50 mg

Purpose

Antihistamine

Uses:

- temporarily relieves these symptoms due to hay fever or other upper respiratory allergies:
- runny nose
- sneezing
- itchy, watery eyes
- itching of the nose or throat
- temporarily relieves these symptons due to common cold:
- runny nose
- sneezing

Do not use

- to make a child sleepy
- With any other product containing Diphenhydramine HCL, even one used on skin

Ask a doctor before use if you have

- glaucoma
- a breathing problem such as emphysema or chronic bronchitis
- trouble urinating due to an enlarged prostate gland

Ask a doctor or pharmacist before use if you are

taking sedatives or tranquilizers.

When using this product

- marked drowsiness may occur
- avoid alcoholic drinks
- alcohol, sedatives and tranquilizers may increase drowsiness
- use caution when driving a motor vehicle or operating machinery
- excitability may occur, especially in children

If pregnant or breast-feeding,

ask a health professional before use.

Keep out of reach of children

In case of overdose, get medical help or contact a Poison Control Center right away (1-800-222-1222)

Directions:

- take every 4 to 6 hours, or as directed by a doctor
- do not exceed 6 doses in 24 hours

adults and children 12 years and over | 1 capsule
children under 12 years | ask a doctor

Other information

- Store at 20-25 °C (68-77 °F)

Inactive ingredients

black iron oxide, D & C Red #28, FD & C Blue #1, FD & C Red #40, gelatin, lactose monohydrate, magnesium stearate, silicon dioxide, sodium lauryl sulfate

Questions or comments?

(866) 933-6337 (Mon-Fri 8 AM to 4 PM EST)

PACKAGE LABEL

welmate

Compare to active ingredient in BENADRYL® Allergy Extra Strength*

ANTIHISTAMINE

Allergy Relief

Diphenhydramine

HCl Capsules, USP 50 mg

For temporary relief of:

Sneezing

Runny nose

Itchy watery eyes

Itchy nose or throat

1000 CAPSULES

THIS PACKAGE FOR HOUSEHOLDS WITHOUT YOUNG CHILDREN